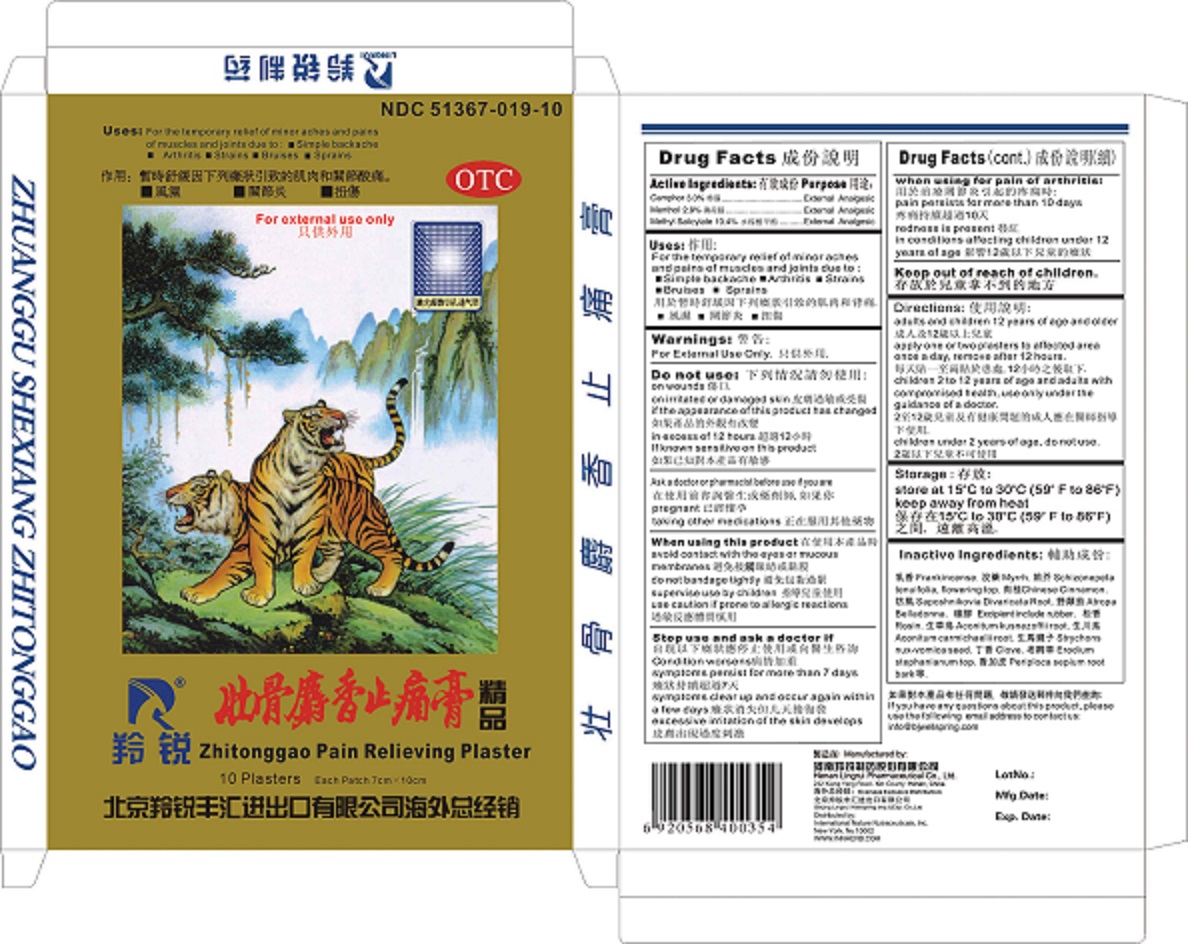 DRUG LABEL: Zhuanggu Shexiang Zhitonggao Pain Relieving Plaster
NDC: 51367-019 | Form: PLASTER
Manufacturer: International Nature Nutraceuticals
Category: otc | Type: HUMAN OTC DRUG LABEL
Date: 20131227

ACTIVE INGREDIENTS: CAMPHOR (NATURAL) 114.29 mg/1 1; MENTHOL 114.29 mg/1 1; METHYL SALICYLATE 85.72 1/1 1
INACTIVE INGREDIENTS: FRANKINCENSE; MYRRH; SCHIZONEPETA TENUIFOLIA FLOWERING TOP; CHINESE CINNAMON; SAPOSHNIKOVIA DIVARICATA ROOT; ATROPA BELLADONNA; NATURAL LATEX RUBBER; ROSIN; ACONITUM KUSNEZOFFII ROOT; ACONITUM CARMICHAELII ROOT; STRYCHNOS NUX-VOMICA SEED; CLOVE; ERODIUM STEPHANIANUM TOP; PERIPLOCA SEPIUM ROOT BARK

Drug Facts

Active Ingredients

Camphor-3.0%
Menthol- 2.9%

Methyl Salicylate- 10.4%

Uses

For the temporary relief of minor aches and pains of muscles and joints due to:

- Simple backache
- Arthritis
- Strains
- Bruises
- Sprains

Warnings:

For External Use Only

Do Not Use

- On wounds
- On irritated or damaged skin
- If the appearance of this product has changed
- In excess of 12 hours
- If known sensitivity this product

Ask a doctor or pharmacist before use if you are:

Pregnant, or taking other medications

Stop Use and ask a doctor if

- Condition worsens
- Symptoms persist for more than 7 days
- Symptoms clear up and occur again within a few days
- Excessive irritation of the skin develops

When Using for pain of arthritis

- Pain persists for more than 10 days
- redness is present
- In conditions affecting children under 12 years of age

Keep Out of Reach of Children

Directions

Adults and Children 12 years of age and older: apply one or two plasters to affected area once a day, remove after 12 hours

Children 2 to 12 years of age and adults with compromised health: use only the guidance of a doctor

Children under 2 years of age: do not use

Storage

Store at 15o C to 30o C (59o to 86o F)

Keep away from heat

Inactive Ingredients

Frankincense, Myrrh, Schizonepeta tenuifolia flowering top, Saposhnikovia divaricata root, Chinese Cinnamon, Atropa belladona, natural latex rubber, rosin, aconitum kusnezoffi root, aconitum carmichaelii root, strychons nux-vomica seed, clove, erodium stephanianum top, periploca sepium root bark